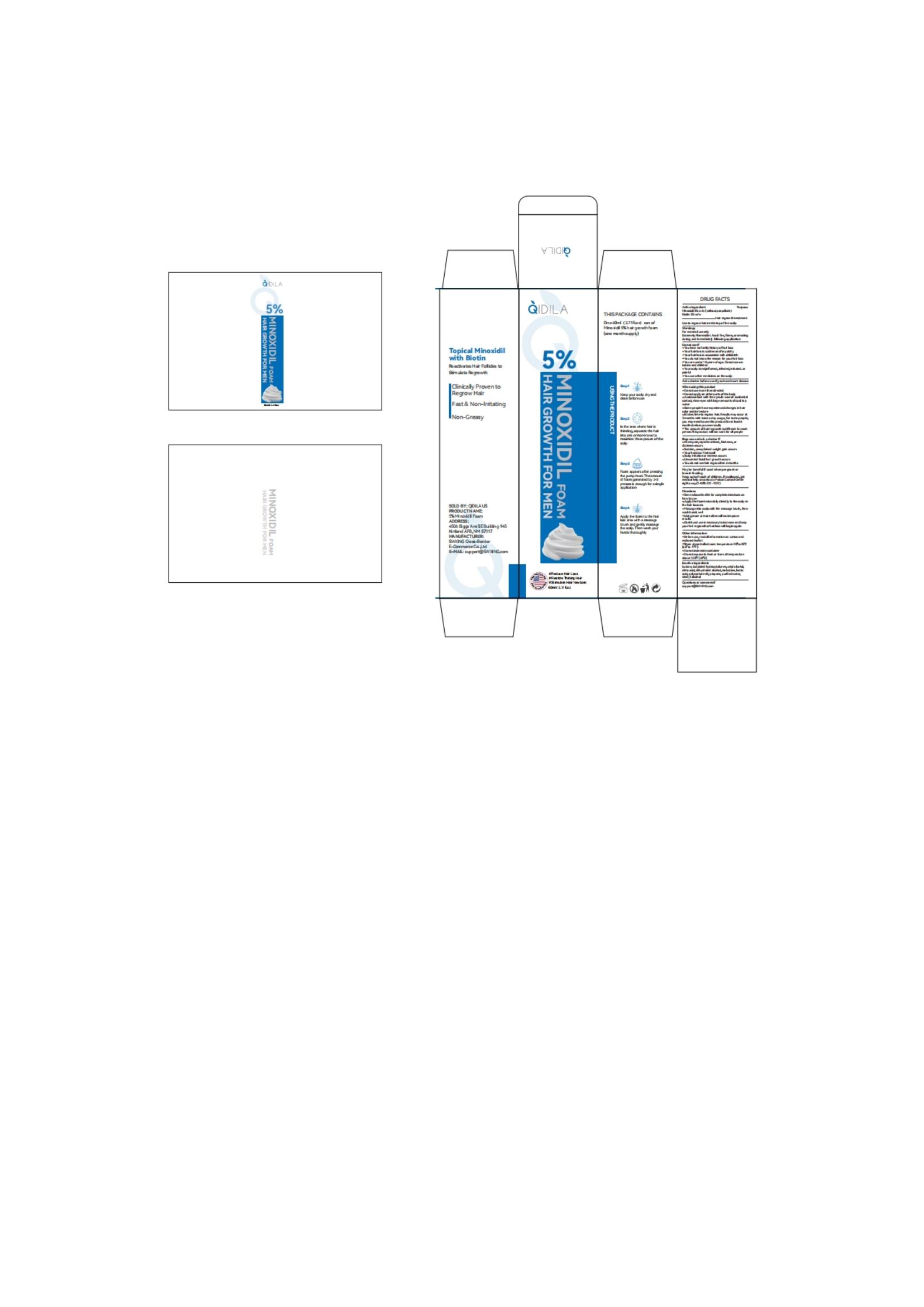 DRUG LABEL: QIDILA 5% Minoxidil foam
NDC: 85212-0036 | Form: AEROSOL, FOAM
Manufacturer: Beijing JUNGE Technology Co., Ltd.
Category: otc | Type: HUMAN OTC DRUG LABEL
Date: 20250513

ACTIVE INGREDIENTS: BIOTIN 5 g/100 mL; MINOXIDIL 5 g/100 mL
INACTIVE INGREDIENTS: CETYL ALCOHOL 1 mL/100 mL; CITRIC ACID 1 mL/100 mL; ISOBUTANE 1 mL/100 mL; WATER 82.5 mL/100 mL; LACTIC ACID 1 mL/100 mL; DEHYDRATED ALCOHOL 1 mL/100 mL; POLYSORBATE 60 1 mL/100 mL; STEARYL ALCOHOL 0.5 mL/100 mL; BUTYLATED HYDROXYTOLUENE 1 mL/100 mL

ALARMS

For external use only.

Extremely Flammable: Avoid fire, flame, or smoking during andimmediately following application.

KEEP OUT OF REACH OF CHILDREN

swallowed, get medical help or contact a Poison Control Center rightaway.(1-800-222-1222)right away.

INACTIVE INGREDIENT

ALCOHOL - GLYCERIN - CETYL ALCOHOL - STEARYL ALCOHOL - POLYSORBATE 80 - ANHYDROUS CITRIC ACID - LACTIC ACID - CASTOR OIL - .ALPHA.-TOCOPHEROL - EDETATE DISODIUM - WATER

STORAGE AND HANDLING

Before use, read all information on carton and enclosed leaflet

Store at controlled room temperature 20° to 25℃ (68° to 77°F).Do not incinerate container, Do not expose to heat or store attemperature abowe 120°F (49°C).

DOSAGE AND ADMINISTRATION

See enclosed leaflet for complete directions on how to use.
Apply half a capful twice daily directly to the scalp in the hair loss area
Massage into scalp with fingers, then wash hands well.
Using more or more often will not improve results.
Continued use is necessary to increase and keep your hair regrowthor hair loss will begin again.

Do not use more than directed.

Do not apply on other parts of the body.

Avoid contact with the eyes, In case of accidental contact, rinse eyeswith large amounts of cool tap water.

For some women, you may need to use this product once a day forat least 6 months before you see results.

The amount of hair regrowth is different for each person. Thisproduct will not work for all women

STOP USE

if chest pain, rapid heartbeat, faintness, or dizziness occurs

if sudden, unexplained weight gain occurs.

if your hands or feet swell.

if scalp irritation or redness occurs.

if unwanted facial hair growth occurs .

if you do not see hair regrowth in 6 months.

DO NOT USE

your degree of hair loss is different than that shown on side of thiscarton because this product may not work for you.

You have no family history of hair loss.

Your hair loss is sudden and/or patchy.

You do not know the reason for your hair loss.

Your hair loss is associated with childbirth.

You are under 18 years of age, Do not use on babies and children,

You use other medicines on the scalp.

Your scalp is red, inflamed, infected, irritated, or painful.

ACTIVE INGREDIENT

Minoxidil 5% Biotin 5%

WARNINGS

For external use only. Extremely Flammable: Avoid fire, flame, or smoking during andimmediately following application.

INDICATIONS AND USAGE

Use to regrow hair on the top of the scalp

PURPOSE

Hair regrowth treatment